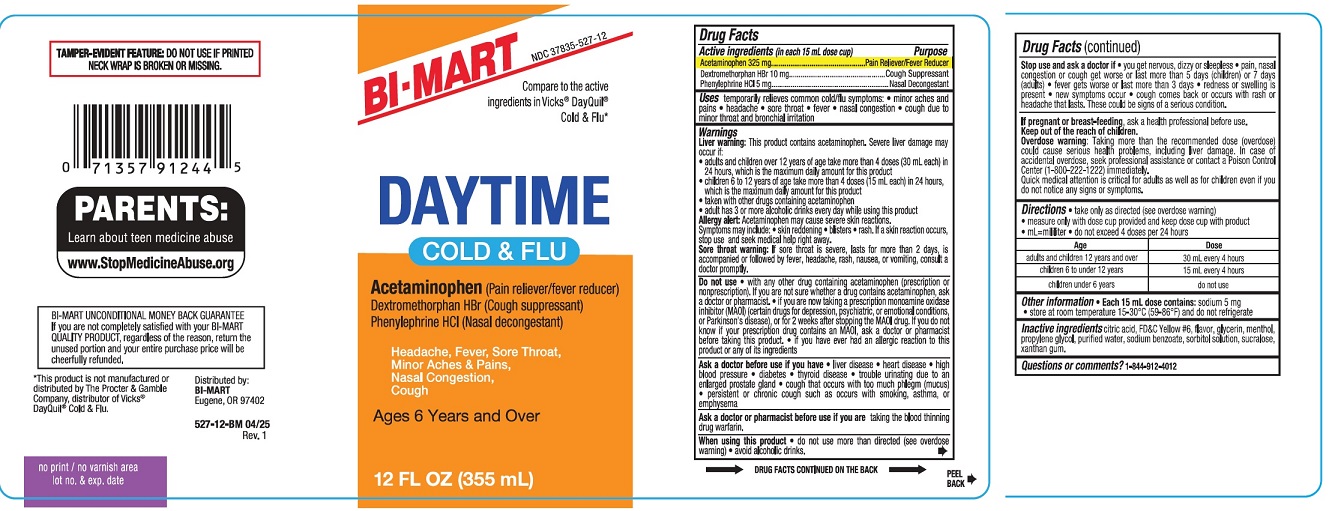 DRUG LABEL: DAYTIME COLD AND FLU
NDC: 37835-527 | Form: LIQUID
Manufacturer: BI-MART
Category: otc | Type: HUMAN OTC DRUG LABEL
Date: 20250501

ACTIVE INGREDIENTS: ACETAMINOPHEN 325 mg/15 mL; DEXTROMETHORPHAN HYDROBROMIDE 10 mg/15 mL; PHENYLEPHRINE HYDROCHLORIDE 5 mg/15 mL
INACTIVE INGREDIENTS: CITRIC ACID; FD&C YELLOW NO. 6; GLYCERIN; MENTHOL; PROPYLENE GLYCOL; WATER; SODIUM BENZOATE; SORBITOL SOLUTION; SUCRALOSE; XANTHAN GUM

DAYTTIME COLD & FLU

Drug Facts

Active ingredients (in each 15 mL dose cup)

Acetaminophen 325 mg

Dextromethorphan HBr 10 mg

Phenylephrine HCl 5 mg

Purpose

Pain reliever/fever reducer

Cough Suppressant

Nasal Decongestant

Uses

temporarily relieves common cold and flu symptoms:

- minor aches and pains
- headache
- sore throat
- fever
- nasal congestion
- cough due to minor throat and bronchial irritation

Warnings

Liver warning:This product contains acetaminophen. Sever liver damage may occur if:

- adults and children over 12 years of age take more than 4 doses (30 mL each) in 24 hours, which is the maximum daily amount for this product
- children 6 to 12 years of age take more than 4 doses (15 mL each) in 24 hours, which is the maximum daily amount for this product
- take with other drug containing acetaminophen
- adult has 3 or more alcoholic drinks every day while using this product

Allergy alert:Acetaminophen may cause sever skin reactions. Symptoms may include:

- skin reddening
- blisters
- ras

If skin reaction occurs, stop use and seek medical help right away.

Sore throat warning:If sore throat is sever, lasts for more than 2 days, is accompanied or followed by fever, headache, rash, nausea, or vomiting, consult a doctor promptly.

Do not use

- with any other products containing acetaminophen (prescription or nonprescription). If you are not sure whether a drug contains acetaminophen, ask a doctor or pharmacist.
- if you are now taking a prescription monoamine oxidase inhibitor (MAOI) (certain drugs for depression, psychiatric or emotional conditions, or Parkinson's diseas), or for 2 weeks after stopping the MAOI drugs. If you do not know if your prescription drug contains an MAOI, ask a doctor or pharmacist before taking this product.
- If you have ever had an allergic reaction to this product or any o its ingredients

Ask a doctor before use if you have

- liver disease
- heart disease
- high blood pressure
- diabete
- thyroid disease
- trouble urinating due to an enlarged prostate gland
- cough accompanied by excessive phlegm (mucus)
- cough that occurs with too much phlegm (mucus)
- persistent or chronic cough such as occurs with smoking, asthma, or emphysema.

Ask a doctor or pharmacist before use if you are

taking the blood thinning drug warfarin.

When using this product

- do not use more than directed (see overdose warning)
- avoid alcoholic drinks

Stop use and ask a doctor if

- you get nervous, dizzy or sleepless
- pain, nasal congestion or cough get worse or last more than 5 days (children) or 7 days (adults)
- fever gets worse or lasts more than 3 days
- redness or swelling is present
- new symptoms occur
- cough comes back, or occurs with rash or headache that lasts. These could be signs of a serious condition.

If pregnant or breast-feeding,

ask a health professional before use.

Keep out of reach of children.

Overdose warning:

Taking more than the recommended dose (overdose) may cause serious health problemas including liver damamge. In case of accidental overdose, seek professional assistance or contact a Poison Control Center (1-800-222-1222) immediately. Quick medical attention is critical for adults as well as for children even if ou do not notice any signs or symptoms.

Directions

- take only as directed (see Overdose warning)
- measure only with dose cup provided and keep dose cup with product
- mL=mililiter
- do not exceed 4 doses per 24 hours

Age | Dose
adults & children 12 years and over | 30 mL every 4 hours
children 6 to under 12 years | 15 mL every 4 hours
children under 6 years | do not use

Other information

- each 15 mL contains:sodium 5 mg
- store at room temperature 15-30°C (59-86°C) and do not refrigerate

Inactive ingredients

Citric acid, FD&C Yellow No 6, flavor, glycerin, menthol, propylene glycol, purified water, sodium benzoate, sorbitol solution, sucralose, xanthan gum

Questions or Comments?

1-844-912-4012